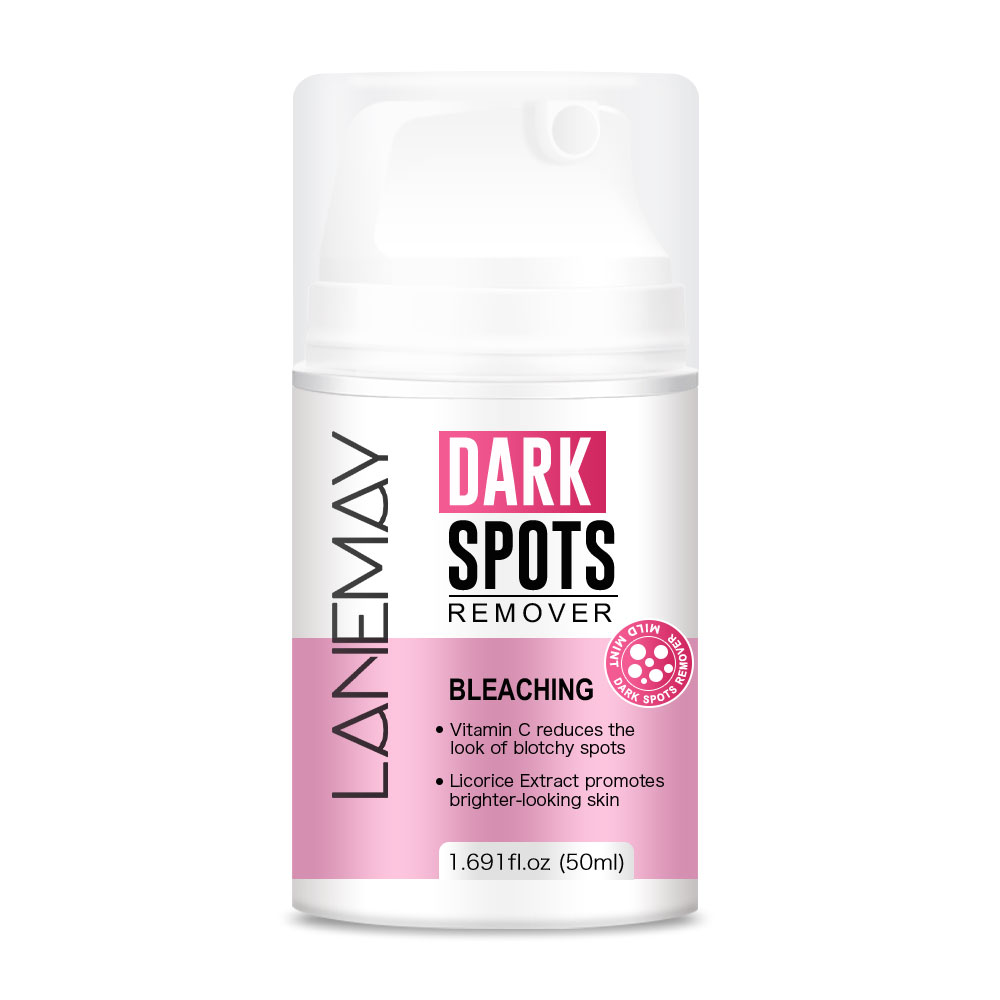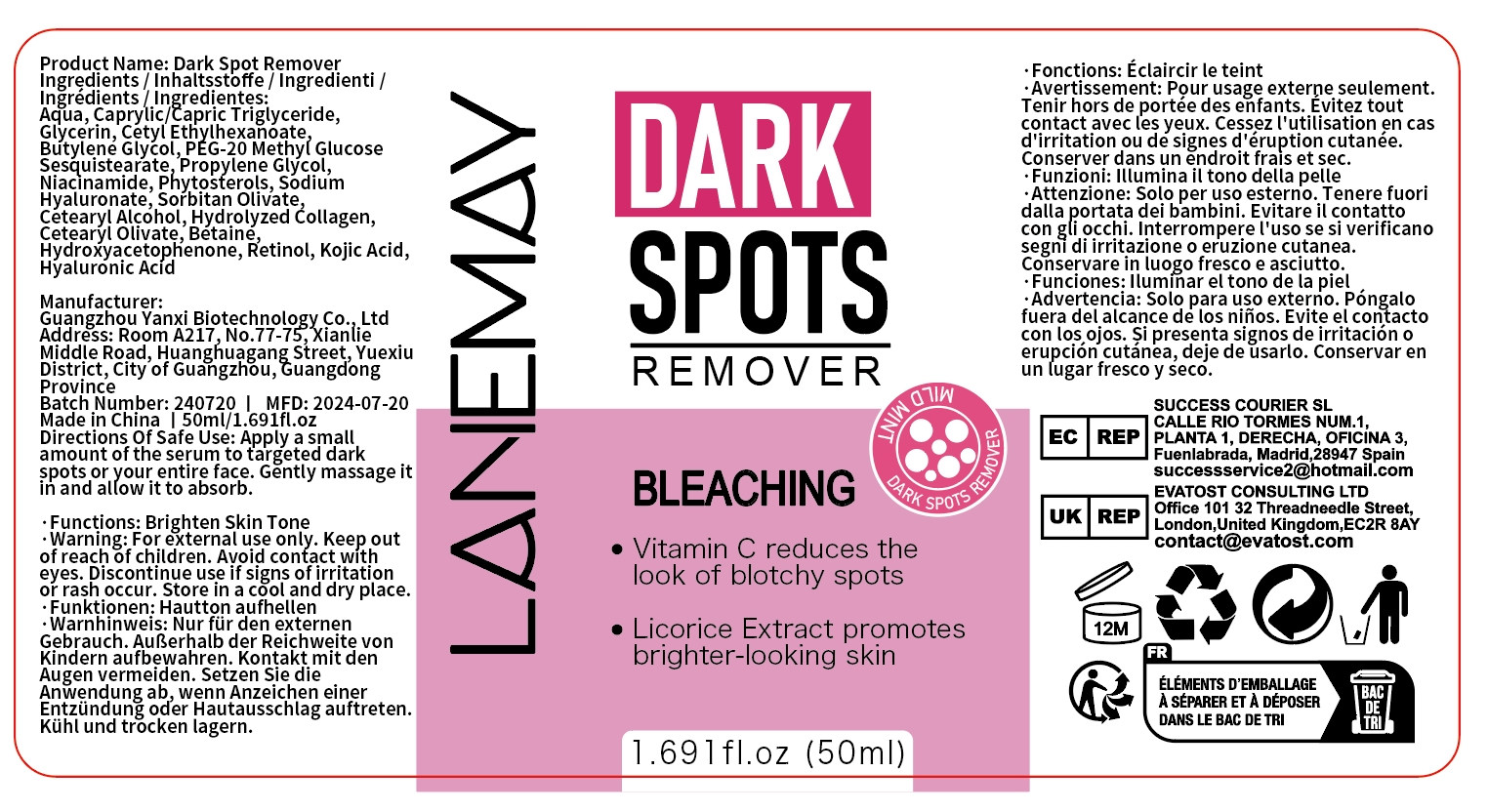 DRUG LABEL: DARK SPOT REMOVER
NDC: 84025-111 | Form: CREAM
Manufacturer: Guangzhou Yanxi Biotechnology Co.. Ltd
Category: otc | Type: HUMAN OTC DRUG LABEL
Date: 20240802

ACTIVE INGREDIENTS: CAPRYLIC/CAPRIC/LAURIC TRIGLYCERIDE 5 mg/50 mL; GLYCERIN 3 mg/50 mL
INACTIVE INGREDIENTS: WATER

DOSAGE AND ADMINISTRATION

Cream for Brightening Skin

WARNINGS

keep out of children

INACTIVE INGREDIENT

Aqua

INDICATIONS AND USAGE

For minimizing dark spots on the skin

keep out of children

PURPOSE

Removes dark spots and brightens the skin